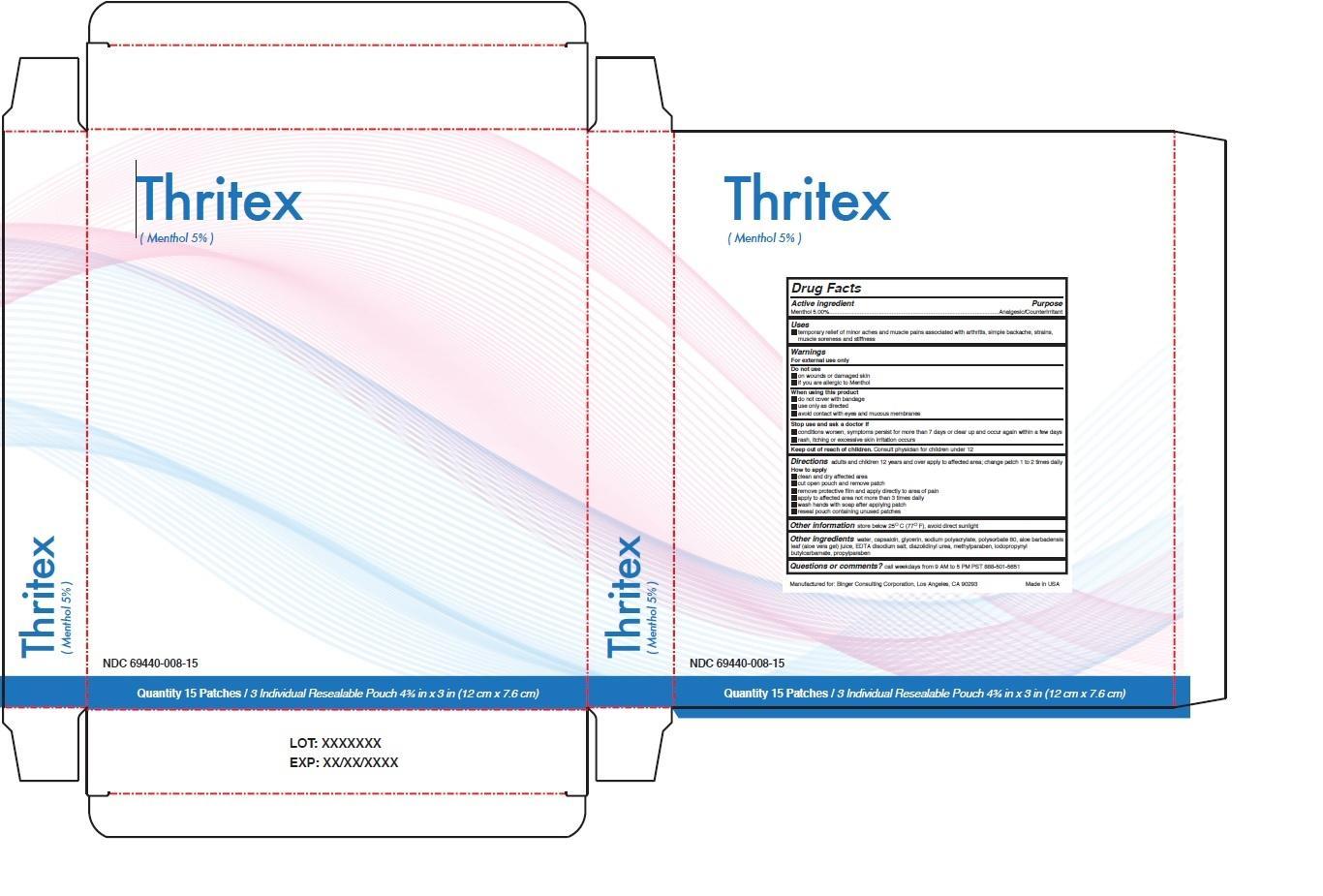 DRUG LABEL: Thritex
NDC: 69440-008 | Form: PATCH
Manufacturer: Binger Consulting Corporation
Category: otc | Type: HUMAN OTC DRUG LABEL
Date: 20241127

ACTIVE INGREDIENTS: MENTHOL, UNSPECIFIED FORM 5 g/100 g
INACTIVE INGREDIENTS: CAPSAICIN; WATER; GLYCERIN; SODIUM POLYACRYLATE (2500000 MW); POLYSORBATE 80; ALOE VERA LEAF; EDETATE DISODIUM; DIAZOLIDINYL UREA; METHYLPARABEN; IODOPROPYNYL BUTYLCARBAMATE; PROPYLPARABEN

Thritex

Active ingredient

Menthol 5.00%

Purpose

Analgesic/Counterirritant

Keep out of reach of children. Consult physician for children under 12.

Uses

• temporary relief of minor aches and muscle pains associated with arthritis, simple backache, strains, muscle soreness and stiffness

Warnings

For external use only

Do not use

• on wounds or damaged skin

• if you are allergic to Menthol

When using this product

• do not cover with bandage

• use only as directed

• avoid contact with eyes and mucous membranes

Stop use and ask a doctor if

• conditions worsen, symptoms persist for more than 7 days or clear up and occur again within a few days

• rash, itching or excessive skin irritation occurs

DOSAGE AND ADMINISTRATION

Directions adults and children 12 years and over apply to affected area; change patch 1 to 2 times daily

How to apply

• clean and dry affected area

• cut open pouch and remove patch

• remove protective film and apply directly to area of pain

• apply to affected area not more than 3 times daily

• wash hands with soap after applying patch

• reseal pouch containing unused patches.

INACTIVE INGREDIENT

Other ingredients water, capsaicin, glycerin, sodium polyacrylate, polysorbate 80, aloe barbadensis leaf (aloe vera leaf) juice, EDTA disodium salt, diazolidinyl urea, methylparaben, iodopropynyl butylcarbamate, propylparaben

Questions or comments? call weekdays from 9 AM to 5 PM PST 888-501-5651

Other information store below 25°C (77°F), avoid direct sunlight